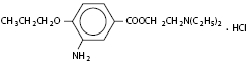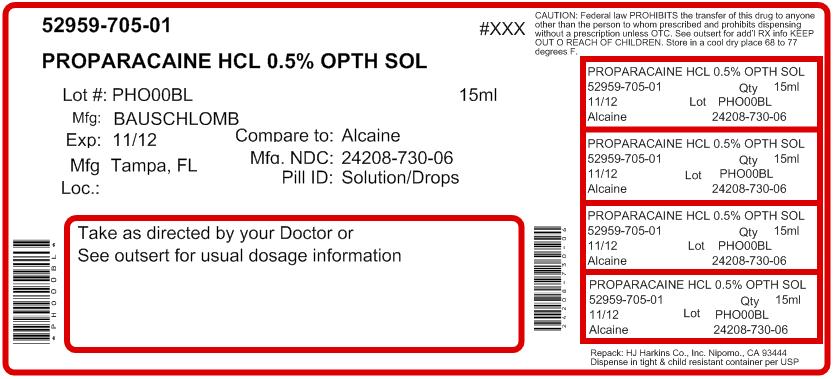 DRUG LABEL: Proparacaine Hydrochloride
                        
NDC: 52959-705 | Form: SOLUTION/ DROPS
Manufacturer: H.J. Harkins Company, Inc.
Category: prescription | Type: HUMAN PRESCRIPTION DRUG LABEL
Date: 20120419

ACTIVE INGREDIENTS: PROPARACAINE HYDROCHLORIDE 5 mg/1 mL
INACTIVE INGREDIENTS: BENZALKONIUM CHLORIDE; GLYCERIN; HYDROCHLORIC ACID; WATER; SODIUM HYDROXIDE

Proparacaine Hydrochloride Ophthalmic Solution USP, 0.5% (Sterile)

Rx only

DESCRIPTION:

Proparacaine Hydrochloride Ophthalmic Solution USP, 0.5% is a topical anesthetic prepared as a sterile aqueous ophthalmic solution. The active ingredient is represented by the following structural formula:

C16H26N2O3 • HCI

Mol. wt.: 330.85

Chemical name: Benzoic acid, 3-amino-4-propoxy-,2-(diethylamino) ethyl ester, monohydrochloride.

Each mL Contains:

ACTIVE: Proparacaine Hydrochloride 5 mg (0.5%); INACTIVES: Glycerin, Hydrochloric Acid, Purified Water. Hydrochloric Acid and/or Sodium Hydroxide may be added to adjust pH (3.5 – 6.0). PRESERVATIVE ADDED: Benzalkonium Chloride 0.01%.

CLINICAL PHARMACOLOGY:

Proparacaine is a rapid acting local anesthetic suitable for ophthalmic use. With a single drop, the onset of anesthesia usually begins within 30 seconds and persists for 15 minutes or longer.

The main site of anesthetic action is the nerve cell membrane where proparacaine interferes with the large transient increase in the membrane permeability to sodium ions that is normally produced by a slight depolarization of the membrane. As the anesthetic action progressively develops in a nerve, the threshold for electrical stimulation gradually increases and the safety factor for conduction decreases. When this action is sufficiently well developed, block of conduction is produced.

The exact mechanism whereby proparacaine and other local anesthetics influence the permeability of the cell membrane is unknown; however, several studies indicate that local anesthetics may limit sodium ion permeability by closing the pores through which the ions migrate in the lipid layer of the nerve cell membrane. This limitation prevents the fundamental change necessary for the generation of the action potential.

INDICATIONS AND USAGE:

Proparacaine hydrochloride ophthalmic solution is indicated for topical anesthesia in ophthalmic practice. Representative ophthalmic procedures in which the preparation provides good local anesthesia include measurement of intraocular pressure (tonometry), removal of foreign bodies and sutures from the cornea, conjunctival scraping in diagnosis and gonioscopic examination; it is also indicated for use as a topical anesthetic prior to surgical operations such as cataract extraction.

CONTRAINDICATIONS:

This preparation is contraindicated in patients with known hypersensitivity to any component of the solution.

WARNINGS:

NOT FOR INJECTION - FOR TOPICAL OPHTHALMIC USE ONLY

Prolonged use of a topical ocular anesthetic may produce permanent corneal opacifiction with accompanying loss of vision.

PRECAUTIONS:

General:

Proparacaine should be used cautiously and sparingly in patients with known allergies, cardiac disease, or hyperthyroidism. The long-term toxicity of proparacaine is unknown; prolonged use may possibly delay wound healing. Although exceedingly rare with ophthalmic application of local anesthetics, it should be borne in mind that systemic toxicity (manifested by central nervous system stimulation followed by depression) may occur.

Protection of the eye from irritating chemicals, foreign bodies and rubbing during the period of anesthesia is very important. Tonometers soaked in sterilizing or detergent solutions should be thoroughly rinsed with sterile distilled water prior to use. Patients should be advised to avoid touching the eye until the anesthesia has worn off. Do not touch dropper tip to any surface as this may contaminate the solution.

Carcinogenesis, Mutagenesis, Impairment of Fertility:

Long-term studies in animals have not been performed to evaluate carcinogenic potential, mutagenicity, or possible impairment of fertility in males or females.

Pregnancy:

Teratogenic Effects: Pregnancy Category C: Animal reproduction studies have not been conducted with proparacaine hydrochloride ophthalmic solution. It is also not known whether proparacaine hydrochloride can cause fetal harm when administered to a pregnant woman or can affect reproduction capacity. Proparacaine hydrochloride should be administered to a pregnant woman only if clearly needed.

Nursing Mothers:

It is not known whether this drug is excreted in human milk. Because many drugs are excreted in human milk, caution should be exercised when proparacaine hydrochloride is administered to a nursing woman.

Pediatric Use:

Controlled clinical studies have not been performed with proparacaine hydrochloride ophthalmic solution to establish safety and effectiveness in pediatric patients; however, the literature cites the use of proparacaine hydrochloride as a topical ophthalmic anesthetic agent in pediatric patients.

ADVERSE REACTIONS:

Pupillary dilation or cycloplegic effects have rarely been observed with proparacaine hydrochloride. The drug appears to be safe for use in patients sensitive to other local anesthetics, but local or systemic sensitivity occasionally occurs. Instillation of proparacaine in the eye at recommended concentration and dosage usually produces little or no initial irritation, stinging, burning, conjunctival redness, lacrimation or increased winking. However, some local irritation and stinging may occur several hours after the instillation.

Rarely, a severe, immediate-type, apparently hyperallergic corneal reaction may occur which includes acute, intense and diffuse epithelial keratitis; a gray, ground-glass appearance; sloughing of large areas of necrotic epithelium; corneal filaments and, sometimes, iritis with descemetitis.

Allergic contact dermatitis with drying and fissuring of the fingertips has been reported.

Softening and erosion of the corneal epithelium and conjunctival congestion and hemorrhage have been reported.

DOSAGE AND ADMINISTRATION:

Deep anesthesia as in cataract extraction:

Instill 1 drop every 5 to 10 minutes for 5 to 7 doses.

Removal of sutures:

Instill 1 or 2 drops 2 or 3 minutes before removal of stitches.

Removal of foreign bodies:

Instill 1 or 2 drops prior to operating.

Tonometry:

Instill 1 or 2 drops immediately before measurement

FOR OPHTHALMIC USE ONLY

HOW SUPPLIED:

Proparacaine Hydrochloride Ophthalmic Solution USP, 0.5% is supplied in a plastic bottle with a controlled drop tip in the following size:

15 mL bottle - Prod. No. 04711

Storage

Refrigerate at 2°-8°C (36°- 46°F). Protect from light. Keep tightly closed.

Do not use if the solution shows more than a faint yellow color.

DO NOT USE IF IMPRINTED NECKBAND IS NOT INTACT.

KEEP OUT OF REACH OF CHILDREN.

Rx only

Bausch & Lomb Incorporated
Tampa, FL 33637
©Bausch & Lomb Incorporated

Revised November 2007

9114400 (Folded)
9114500 (Flat)

Principal Display Panel

NDC 24208-730-06

Bausch & Lomb

Proparacaine Hydrochloride Ophthalmic Solution USP, 0.5% (Sterile)

Rx only

[icon- eye] [icon- 0.5%] [icon-solution] [icon- 15 mL]

Repacked by:

H.J. Harkins Company, Inc.

Nipomo, CA 93444